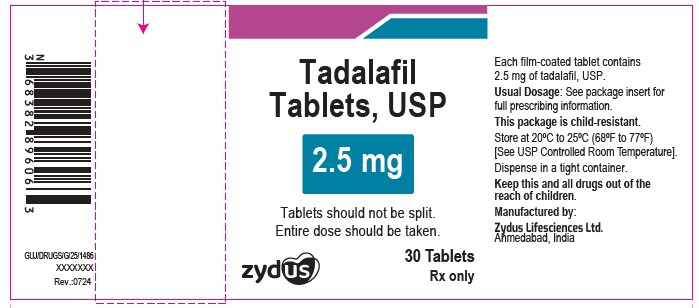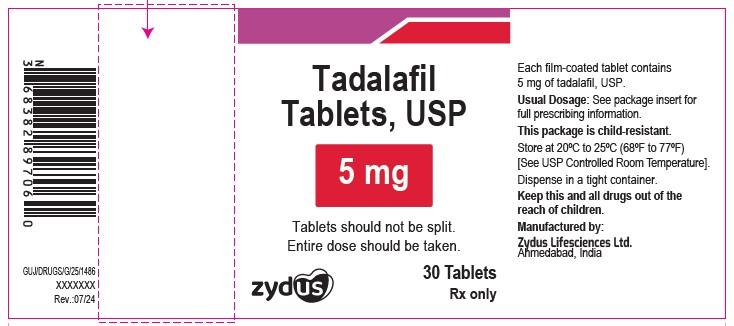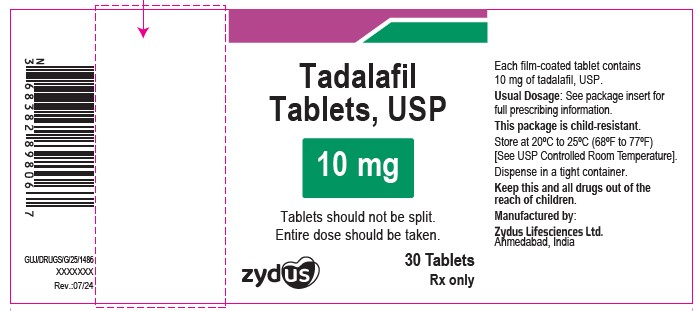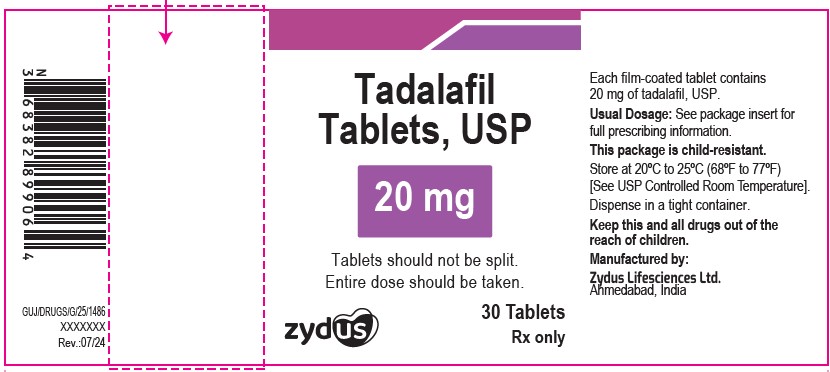 DRUG LABEL: Tadalafil
NDC: 70771-1475 | Form: TABLET, FILM COATED
Manufacturer: Zydus Lifesciences Limited
Category: prescription | Type: HUMAN PRESCRIPTION DRUG LABEL
Date: 20240812

ACTIVE INGREDIENTS: TADALAFIL 2.5 mg/1 1
INACTIVE INGREDIENTS: CELLULOSE, MICROCRYSTALLINE; CROSCARMELLOSE SODIUM; HYDROXYPROPYL CELLULOSE, UNSPECIFIED; HYPROMELLOSES; LACTOSE MONOHYDRATE; MAGNESIUM STEARATE; TALC; TITANIUM DIOXIDE; TRIACETIN

TADALAFIL TABLETS

PACKAGE LABEL.PRINCIPAL DISPLAY PANEL

NDC 70771-1475-3 in bottle of 30 tablets

Tadalafil Tablets USP, 2.5 mg

Rx Only

30 tablets

NDC 70771-1476-3 in bottle of 30 tablets

Tadalafil Tablets USP, 5 mg

Rx Only

30 tablets

NDC 70771-1477-3 in bottle of 30 tablets

Tadalafil Tablets USP, 10 mg

Rx Only

30 tablets

NDC 70771-1478-3 in bottle of 30 tablets

Tadalafil Tablets USP, 20 mg

Rx Only

30 tablets